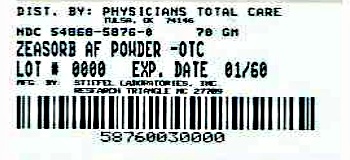 DRUG LABEL: Zeasorb
NDC: 54868-5876 | Form: POWDER
Manufacturer: Physicians Total Care, Inc.
Category: otc | Type: HUMAN OTC DRUG LABEL
Date: 20120523

ACTIVE INGREDIENTS: MICONAZOLE NITRATE 20.6 mg/1 g
INACTIVE INGREDIENTS: ACRYLAMIDE; ALDIOXA; CHLOROXYLENOL; IMIDUREA; POWDERED CELLULOSE; TALC

Drug Facts

Active ingredient

Miconazole nitrate 2%

Purpose

antifungal

Use (Athlete's Foot)

for the cure of most athlete's foot

Warnings

For external use only

Do not use

- on children under 2 years of age unless directed by a doctor.

Avoid contact with the eyes.

Stop use and ask a doctor if (Athlete's Foot)

- irritation occurs or there is no improvement within 4 weeks.

Keep out of reach of children.

If swallowed, get medical help or contact a Poison Control Center right away.

Directions (Athlete's Foot)

- Clean the affected area and dry thoroughly.
- Apply a thin layer of the product over affected area twice daily (morning and night) or as directed by a doctor.
- Supervise children in the use of this product.
- Pay special attention to spaces between the toes; wear well-fitting, ventilated shoes, and change shoes and socks at least once daily.
- Use daily for 4 weeks.
- If condition persists longer, consult a doctor.
- This product is not effective on the scalp or nails.

Other information

Product settles during shipment. Package contains full net weight.

Inactive ingredients

acrylamide/sodium acrylate copolymer, aldioxa, chloroxylenol, fragrance, imidurea, microporous cellulose, talc. Contains no starch.

Questions?

call 1-888-438-7426. Side effects should be reported to this number.

Manufactured for: Stiefel Laboratories, Inc. Research Triangle Park, NC 27709

www.zeasorb.com

IRONMAN® is a registered trademark of World Triathlon Corporation used herein by permission.

ZEASORB is a registered trademark of Stiefel Laboratories, Inc.

Additional barcode labeling by:
Physicians Total Care, inc.
Tulsa, Oklahoma 74146

Principal Display Panel

NDC 54868-5876-0

Zeasorb®

ANTIFUNGAL TREATMENT

Miconazole Nitrate 2%

Super Absorbent Powder

cures most

athlete's foot

Relieves:

- Itching
- Burning
- Scaling

Official Partner IRONMAN®

Net Wt. 2.5 Oz (71g)